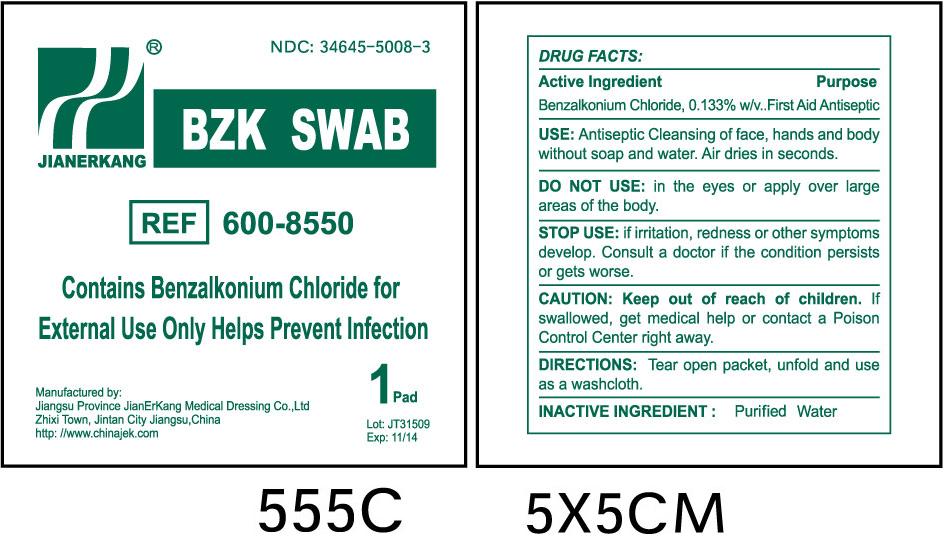 DRUG LABEL: BZK
NDC: 34645-5008 | Form: SWAB
Manufacturer: Jianerkang Medical Co., Ltd
Category: otc | Type: HUMAN OTC DRUG LABEL
Date: 20231023

ACTIVE INGREDIENTS: BENZALKONIUM CHLORIDE 1.33 mg/1 mL
INACTIVE INGREDIENTS: WATER

Drug Facts

Active Ingredient

Benzalkonium Chloride, 0.133% w/v

Purpose

First Aid Antiseptic

INDICATIONS AND USAGE

Antiseptic Cleansing of face, hands and body without soap and water, Air dries in seconds. USE:

WARNINGS

DO NOT USE:

in the eyes or apply over larger area of the body.

STOP USE:

if irritation, redness or other symptoms develop. Consult a doctor if the condition persists or gets worse.

KEEP OUT OF REACH OF CHILDREN

If swallowed, get medical help or contact a Poison Control Center right away. CAUTION: Keep out of reach of children.

DOSAGE AND ADMINISTRATION

Tear open packet, unfold and use as a washcloth. DIRECTIONS:

Purified Water INACTIVE INGREDIENTS: